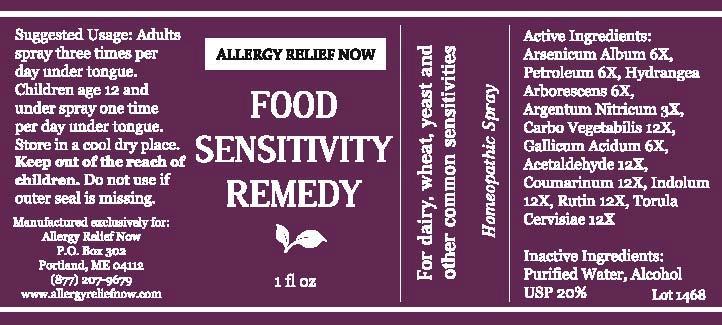 DRUG LABEL: Allergy Relief Now Food Sensitivity Remedy
NDC: 61727-051 | Form: SPRAY
Manufacturer: Homeocare Laboratories
Category: homeopathic | Type: HUMAN OTC DRUG LABEL
Date: 20140324

ACTIVE INGREDIENTS: ARSENIC TRIOXIDE 6 [hp_X]/1 [hp_X]; KEROSENE 6 [hp_X]/1 [hp_X]; HYDRANGEA ARBORESCENS ROOT 6 [hp_X]/1 [hp_X]; SILVER NITRATE 3 [hp_X]/1 [hp_X]; ACTIVATED CHARCOAL 12 [hp_X]/1 [hp_X]; GALLIC ACID MONOHYDRATE 6 [hp_X]/1 [hp_X]; ACETALDEHYDE 12 [hp_X]/1 [hp_X]; COUMARIN 12 [hp_X]/1 [hp_X]; INDOLE 12 [hp_X]/1 [hp_X]; RUTIN 12 [hp_X]/1 [hp_X]; SACCHAROMYCES CEREVISIAE 12 [hp_X]/1 [hp_X]
INACTIVE INGREDIENTS: WATER; ALCOHOL

Active Ingredients:

Arsenicum Album 6X, Petroleum 6X, Hydrangea Arborscens 6X, Argentum Nitricum 3X, Carbo Vegetabilis 12X, Gallicum Acidum 6X, Acetaldehyde 12X, Coumarinum 12X, Indolum 12X, Rutin 12X, Torula Cervisiae 12X

Suggested Usage:

Adults spray three times per day under tongue. Children age 12 and under spray one time a day under tongue. Store in a cool dry place.

Inactive Ingredients:

Purified Water, Alcohol USP 20%

INDICATIONS AND USAGE

For dairy, wheat, yeast and other common sensitivities Homeopathic Spray

Keep out of the reach of children

Do not use if seal is missing

Allergy Relief Now Food Sensitivity Remedy 1 fl oz

Concordia_LabelFinal-food-1468.jpg